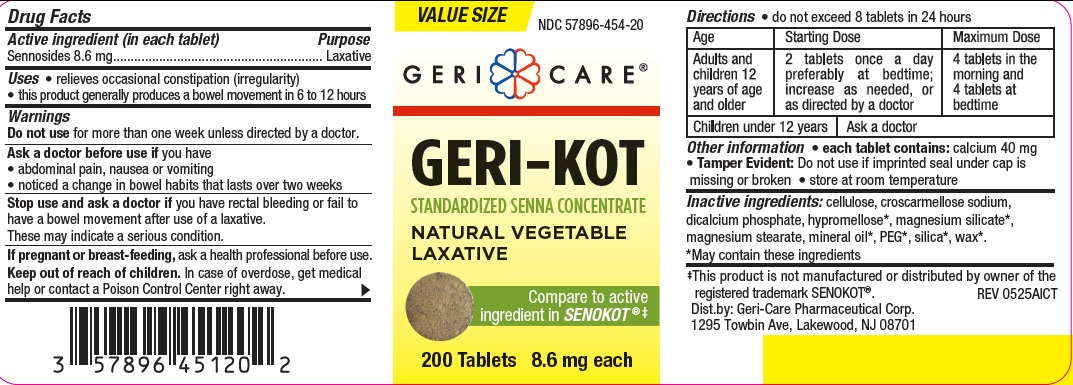 DRUG LABEL: Geri-kot
NDC: 57896-454 | Form: TABLET
Manufacturer: Geri-Care Pharmaceutical Corp
Category: otc | Type: HUMAN OTC DRUG LABEL
Date: 20251204

ACTIVE INGREDIENTS: SENNOSIDES 8.6 mg/1 1
INACTIVE INGREDIENTS: SILICON DIOXIDE; CELLULOSE, MICROCRYSTALLINE; CROSCARMELLOSE SODIUM; CALCIUM PHOSPHATE, DIBASIC, ANHYDROUS; MAGNESIUM SILICATE; MAGNESIUM STEARATE; MINERAL OIL; POLYETHYLENE GLYCOL, UNSPECIFIED; HYPROMELLOSES; CARNAUBA WAX

gc 454

Active ingredient (in each tablet)

Sennosides 8.6 mg

Purpose

Laxative

Uses

- relieves occasional constipation (irregularity)

- generally produces bowel movement in 6 to 12 hours

Warnings

Do not use

for more than 1 week unless directed by a doctor.

Ask a doctor before use if you

- have abdominal pain, nausea or vomiting
- have noticed a sudden change in bowel habits that lasts over 2 weeks

Stop use and ask a doctor if you have rectal bleeding or fail to
have a bowel movement after use of a laxative.
These may indicate a serious condition .

If pregnant or breast-feeding,

ask a health professional before use.

Keep out of reach of children. In case of overdose, get medical help or contact a Poison Control Center right away.

Directions

• do not exceed 8 tablets in 24 hours

Age | Starting Dose | Maximum Dose
adults and children 12 years of age and older | 2 tablets once a day preferably at bedtime; increase as needed, or as directed by a doctor | 4 tablets in the morning and 4 tablets at bedtime
children under 12 years | ask a doctor

Other information

- each tablet contains: calcium 40 mg
- Tamper Evident: Do not use if imprinted seal under cap is missing or broken
- store at room temperature

Inactive ingredients

cellulose, croscarmellose sodium,
dicalcium phosphate, hypromellose*, magnesium silicate*,
magnesium stearate, mineral oil*, PEG*, silica*, wax*.
*May contain these ingredients